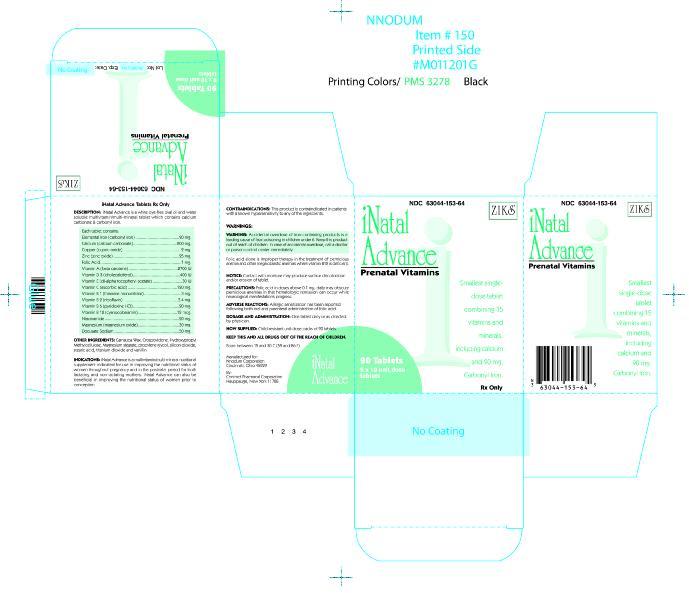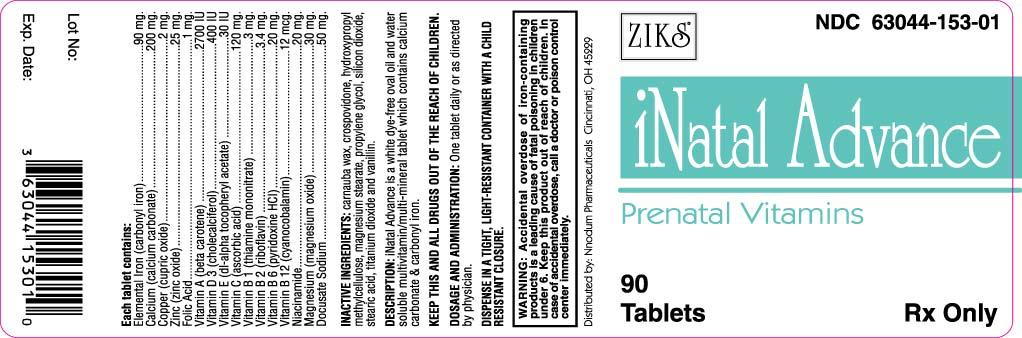 DRUG LABEL: INATAL ADVANCE
NDC: 63044-153 | Form: TABLET, COATED
Manufacturer: Nnodum Pharmaceuticals
Category: prescription | Type: HUMAN PRESCRIPTION DRUG LABEL
Date: 20091026

ACTIVE INGREDIENTS: VITAMIN A 2700 [iU]/1 1; ASCORBIC ACID 120 mg/1 1; CALCIUM CARBONATE 200 mg/1 1; IRON PENTACARBONYL 90 mg/1 1; CHOLECALCIFEROL 400 [iU]/1 1; ALPHA-TOCOPHEROL ACETATE 30 [iU]/1 1; THIAMINE MONONITRATE 3 mg/1 1; RIBOFLAVIN 3.4 mg/1 1; NIACINAMIDE 20 mg/1 1; PYRIDOXINE HYDROCHLORIDE 20 mg/1 1; FOLIC ACID 1 mg/1 1; CYANOCOBALAMIN 12 ug/1 1; ZINC OXIDE 25 mg/1 1; CUPRIC OXIDE 2 mg/1 1; MAGNESIUM OXIDE 30 mg/1 1; DOCUSATE SODIUM 50 mg/1 1
INACTIVE INGREDIENTS: CARNAUBA WAX; CROSPOVIDONE; HYDROXYPROPYL CELLULOSE; MAGNESIUM STEARATE; PROPYLENE GLYCOL; SILICON DIOXIDE; STEARIC ACID; TITANIUM DIOXIDE; ETHYL VANILLIN

INATAL ADVANCE Tablet
63044-153-64

Prenatal multivitamin/multimineral tablet
combining 15 vitamins and minerals,
including calcium and carbonyl iron.

Rx Only

WARNING: Accidental overdose of iron containing prod-ucts is a leading cause of fatal poisoning in children under 6. Keep this product out of the reach of children. In case of accidental overdose, call a doctor or poison controll center immediately.

DESCRIPTION

INATAL Advanced ® is a white, dye-free, oval shaped, oil-and-water soluble multivitamin/multimineral tablet which contains calcium carbonate and carbonyl iron.

Each tablet contains:

Vitamin A (as beta-carotene) . . . . . . . . . . . 2700 I.U.

Vitamin C (ascorbic acid) . . . . . . . . . . . . . . 120 mg

Calcium (as calcium carbonate) . . . . . . . . . . 200 mg

Elemental Iron (as carbonyl iron) . . . . . . . . . . 90 mg

Vitamin D3 (cholecalciferol) . . . . . . . . . . . . 400 I.U.

Vitamin E (dl-alpha tocopheryl acetate) . . . . . 30 I.U.

Vitamin B1 (as thiamine mononitrate) . . . . . . . . 3 mg

Vitamin B2 (riboflavin, USP) . . . . . . . . . . . . . 3.4 mg

Niacinamide . . . . . . . . . . . . . . . . . . . . . . . . 20 mg

Vitamin B6 (as pyridoxine HCI, USP) . . . . . . . 20 mg

Folic Acid, USP . . . . . . . . . . . . . . . . . . . . . . . 1 mg

Vitamin B12 (cyanocobalamin) . . . . . . . . . . . 12 mcg

Zinc (as zinc oxide, USP) . . . . . . . . . . . . . . . . 25 mg

Copper (as cupric oxide) . . . . . . . . . . . . . . . . . 2 mg

Magnesium (as magnesium oxide, USP) . . . . . 30 mg

Docusate Sodium . . . . . . . . . . . . . . . . . . . . 50 mg

INACTIVE INGREDIENTS: Carnauba wax, crospovidone, ethyl vanillin, hydroxypropyl methylcellulose, magnesium stearate, polyethylene glycol, silicon dioxide, stearic acid, and titanium dioxide

INDICATIONS:

INATAL ADVANCE ® is a multivitamin/multimineral nutritional supplement indicated for use in improving the nutritional status of women throughout pregnancy and in the postnatal period for both lactating and nonlactating mothers. INATAL Advanced® can also be beneficial in improving the nutritional status of women prior to conception.

CONTRAINDICATIONS:

This product is contraindicated in patients with a known hypersensitivity to any of the ingredients.

WARNINGS:

Folic acid alone is improper therapy in the treatment of pernicious anemia and other megaloblastic anemias where vitamin B12 is deficient.

NOTICE: Contact with moisture may produce surface discoloration or erosion of the tablet.

PRECAUTIONS:

Folic acid in doses above 0.1mg daily may obscure pernicious anemia in that hematologic remission can occur while neurological manifestations progress.

PEDIATRIC USE:

Safety and effectiveness in pediatric patients have not been established

.

GERIATRIC USE:

Clinical studies on this product have not been performed in sufficient numbers of subjects aged 65 and over to determine whether elderly subjects respond differently from younger subjects. In general, dose selection for an elderly patient should be cautious, usually staring at the low end of the dosing range, reflecting the greater frequency of decreased hepatic, renal, or cardiac function, and of concomitant disease or other drug therapy.

DOSAGE AND ADMINISTRATION:

One tablet daily or as directed by a physician.

HOW SUPPLIED:

NDC 63044-153-64 Unit Dose Packs of 90’s with each blister card containing 10 tablets per card.

Store at controlled room temperature 15°- 30°C (59°-86°F).

KEEP THIS AND ALL DRUGS OUT OF THE REACH OF CHILDREN.

Manufactured For
Nnodum Pharmaceuticals
Cincinnati, Ohio 45229